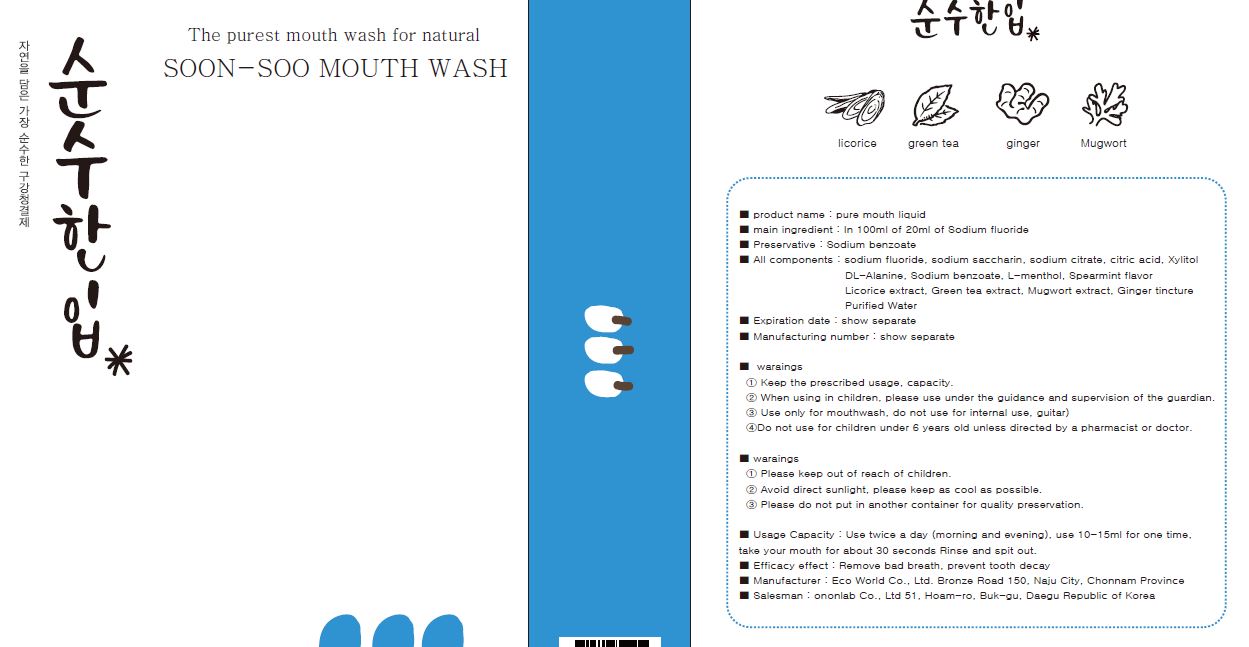 DRUG LABEL: Pure Mouth Liquid
NDC: 72875-0001 | Form: LIQUID
Manufacturer: On On Co., Ltd.
Category: otc | Type: HUMAN OTC DRUG LABEL
Date: 20190209

ACTIVE INGREDIENTS: SODIUM FLUORIDE 0.02 g/100 mL
INACTIVE INGREDIENTS: POTASSIUM SODIUM SACCHARATE; SODIUM CITRATE; WATER

Drug Facts

ACTIVE INGREDIENT

sodium fluoride

INACTIVE INGREDIENT

Sodium fluoride
Sodium saccharin
DL-Alanine
Citric acid
Sodium citrate
Xylitol
Green extract
Licorice extract
Mugwort extract
Ginger Tincture
Sodium benzoate
l-menthol
Spearmint flavor
Purified water

PURPOSE

Remove bad breath, prevent tooth decay

keep out of reach of the children

INDICATIONS AND USAGE

Use twice a day (morning and evening), use 10-15ml for one time,
take your mouth for about 30 seconds Rinse and spit out

WARNINGS

Keep the prescribed usage, capacity.
When using in children, please use under the guidance and supervision of the guardian.
Use only for mouthwash, do not use for internal use, guitar)
Do not use for children under 6 years old unless directed by a pharmacist or doctor.

DOSAGE AND ADMINISTRATION

for oral use only